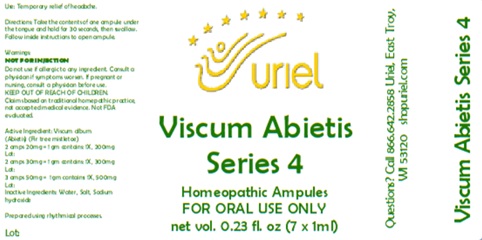 DRUG LABEL: Viscum Abietis Series 4 7ml
NDC: 48951-9266 | Form: LIQUID
Manufacturer: Uriel Pharmacy Inc.
Category: homeopathic | Type: HUMAN OTC DRUG LABEL
Date: 20260203

ACTIVE INGREDIENTS: VISCUM ALBUM FRUITING TOP 1 [hp_X]/1 mL
INACTIVE INGREDIENTS: SODIUM CHLORIDE; SODIUM HYDROXIDE; WATER

Viscum Abietis Series 4 7ml

PURPOSE

Use: Temporary relief of headache.

INDICATIONS AND USAGE

FOR ORAL USE ONLY

DOSAGE AND ADMINISTRATION

Directions: Take the contents of one ampule under the tongue and hold for 30 seconds, then swallow. Follow inside instructions to open ampule.

Warnings:
NOT FOR INJECTION
Do not use if allergic to any ingredient. Consult a physician if symptoms worsen. If pregnant or nursing, consult a physician before use.
Claims based on traditional homepathic practice, not accepted medical evidence. Not FDA evaluated.

KEEP OUT OF REACH OF CHILDREN.

Active Ingredient: Viscum Abietis (Fir tree mistletoe) 2 amps 20mg = 1 gm contains: 1X, 200mg, 2 amps 30mg = 1 gm contains: 1X, 300mg, 3 amps 50mg = 1 gm contains: 1X, 500mg

Inactive Ingredients: Water, Salt, Sodium Hydroxide

Prepared using rhythmical processes.

QUESTIONS

Questions? Call 866.642.2858 Uriel, East Troy, WI 53120 shopuriel.com Lot: